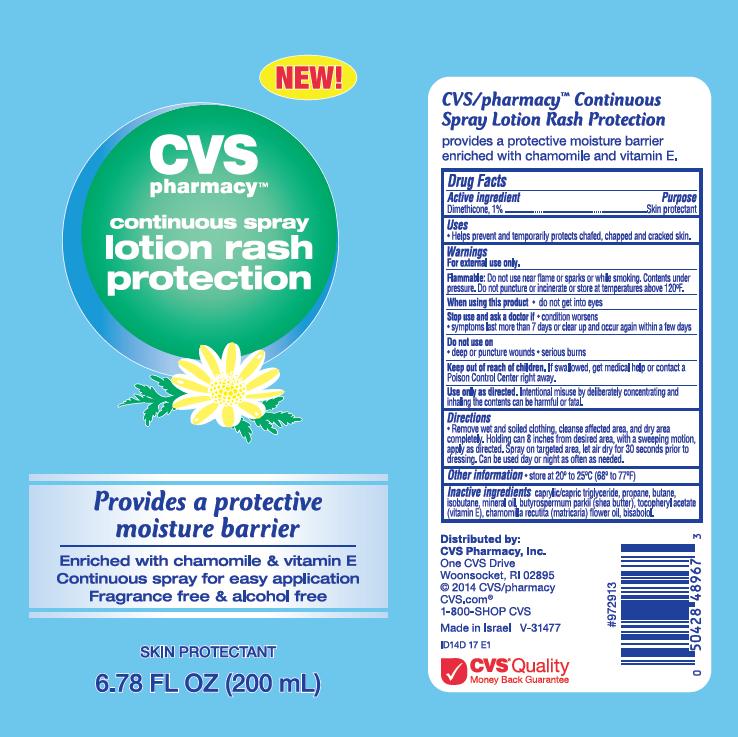 DRUG LABEL: CVS Simple Care Protective Rash
NDC: 59779-142 | Form: SPRAY
Manufacturer: CVS Pharmacy
Category: otc | Type: HUMAN OTC DRUG LABEL
Date: 20140505

ACTIVE INGREDIENTS: DIMETHICONE 1 g/100 mL
INACTIVE INGREDIENTS: MEDIUM-CHAIN TRIGLYCERIDES; PROPANE; BUTANE; ISOBUTANE; MINERAL OIL; SHEA BUTTER; .ALPHA.-TOCOPHEROL ACETATE; CHAMOMILE FLOWER OIL; LEVOMENOL

CVS pharmacy™ continuous spray lotion rash protection

Active ingredient

Dimethicone, 1.0%

Purpose

Skin protectant

Uses

- Helps prevent and temporarily protects chafed, chapped and cracked skin.

Warnings

For external use only.

Flammable:

Do not use near flame or sparks or while smoking. Contents under pressure. Do not puncture or incinerate or store at temperatures above 120°F.

When using this product

- do not get into eyes

Stop use and ask a doctor if

- condition worsens
- symptoms last more than 7 days or clear up and occur again within a few days

Do not use on

- deep or puncture wounds
- serious burns

Keep out of reach of children.

If swallowed, get medical help or contact a Poison Control Center right away.

Use only as directed.

Intentional misuse by deliberately concentrating and inhaling the contents can be harmful or fatal.

Directions

- Remove wet and soiled clothing, cleanse affected area, and dry area completely. Holding can 8 inches from desired area, with a sweeping motion, apply as directed. Spray on targeted area, let air dry for 30 seconds prior to dressing. Can be used day or night as often as needed.

Other Information

- store at 20° to 25°C (68° to 77°F)

Inactive Ingredients

caprylic/capric triglyceride, propane, butane, isobutene, mineral oil, butyrospermum parkii (shea butter), tocopheryl acetate (vitamin E), chamomilla recutita (matricaria) flower oil, bisabolol.

Package/Label Principal Display Panel - Carton Label

CVS pharmacy™
continuous spray lotion rash protection

Provides a protective moisture barrier

Enriched with chamomile & vitamin E
Continuous spray for easy application
Fragrance free & alcohol free

Skin Protectant

6.78 FL OZ (200 mL)

CVS/pharmacy™ Continuous Spray Lotion Rash Protection provides a protective moisture barrier enriched with chamomile and vitamin E.

Distributed by:
CVS Pharmacy, Inc.
One CVS Drive
Woonsocket, RI 02895
© 2014 CVS/pharmacy
CVS.com®
1-800-SHOP CVS

Made in Israel V-31477
ID14D 17 E1

CVS® Quality
Money Back Guarantee

Container Label